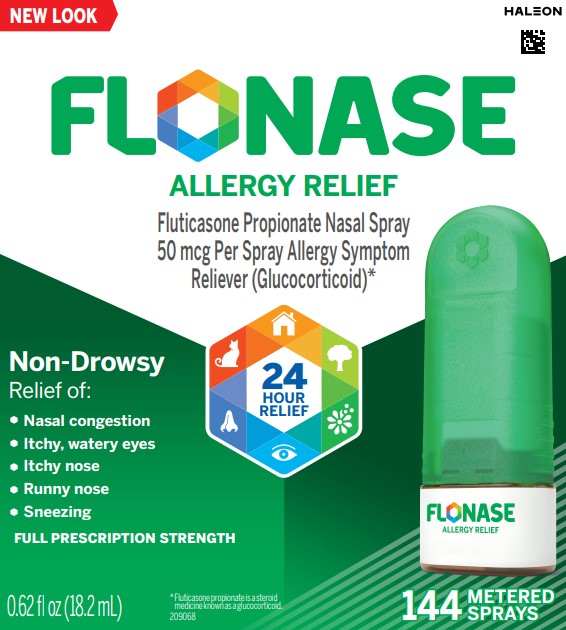 DRUG LABEL: FLONASE
NDC: 0135-0576 | Form: SPRAY, METERED
Manufacturer: Haleon US Holdings LLC
Category: otc | Type: HUMAN OTC DRUG LABEL
Date: 20241219

ACTIVE INGREDIENTS: FLUTICASONE PROPIONATE 50 ug/1 1
INACTIVE INGREDIENTS: BENZALKONIUM CHLORIDE; DEXTROSE, UNSPECIFIED FORM; MICROCRYSTALLINE CELLULOSE; PHENYLETHYL ALCOHOL; POLYSORBATE 80; WATER; CARBOXYMETHYLCELLULOSE SODIUM, UNSPECIFIED

Drug Facts

Active Ingredient (in each spray)

Fluticasone propionate (glucocorticoid)* 50 mcg
*read the Question & Answer Leaflet

Purpose

Allergy symptom reliever

Uses

Temporarily relieves these symptoms of hay fever or other upper respiratory allergies:

- nasal congestion
- itchy nose
- runny nose
- itchy, watery eyes
- sneezing

Warnings

Only for use in the nose. Do not spray into your eyes or mouth.

Do not use

- in children under 4 years of age
- to treat asthma
- if you have an injury or surgery to your nose that is not fully healed
- if you have ever had an allergic reaction to this product or any of the ingredients

Ask a doctor before use if you

have or had glaucoma or cataracts

Ask a doctor or pharmacist before use if you are taking

- medicine for HIV infection (such as ritonavir)
- a steroid medicine for asthma, allergies or skin rash
- ketoconazole pills (medicine for fungal infection)

When using this product

- the growth rate of some children may be slower
- stinging or sneezing may occur for a few seconds right after use
- do not share this bottle with anyone else as this may spread germs
- remember to tell your doctor about all the medicines you take, including this one

Stop use and ask a doctor if

- you have, or come into contact with someone who has, chicken pox, measles or tuberculosis
- your symptoms do not get better within 7 days of starting use or you get new symptoms such as severe facial pain or thick nasal discharge. You may have something more than allergies, such as an infection.
- you get a constant whistling sound from your nose. This may be a sign of damage inside your nose.
- you get an allergic reaction to this product. Seek medical help right away.
- you get new changes to your vision that develop after starting this product
- you have severe or frequent nosebleeds

If pregnant or breast –feeding,

ask a health professional before use.

Keep out of reach of children.

In case of overdose, get medical help or contact a Poison Control Center right away.

Directions

- read the Quick Start Guide for how to:
  - prime the bottle
  - use the spray
  - clean the spray nozzle
- shake gently before each use
- use this product only once a day
- do not use more than directed

ADULTS AND CHILDREN 12 YEARS OF AGE AND OLDER

- Week 1- use 2 sprays in each nostril once daily
- Week 2 through 6 months- use 1 or 2 sprays in each nostril once daily, as needed to treat your symptoms
- After 6 months of daily use – ask your doctor if you can keep using

CHILDREN 4 TO 11 YEARS OF AGE

- the growth rate of some children may be slower while using this product. Children should use for the shortest amount of time necessary to achieve symptom relief. Talk to your child’s doctor if your child needs to use the spray for longer than two months a year.
- an adult should supervise use
- use 1 spray in each nostril once daily

CHILDREN UNDER 4 YEARS OF AGE

- do not use

Other information

- you may start to feel relief the first day and full effect after several days of regular, once-a-day use
- store between 4° and 30°C (39° and 86°F)
- keep this label and enclosed materials. They contain important additional information.

Inactive ingredients

benzalkonium chloride, dextrose, microcrystalline cellulose, phenylethylalcohol, polysorbate 80, purified water, sodium carboxymethylcellulose

Questions or comments?

call toll-free 1-844-FLONASE (1-844-356-6273)

Generic Section

What problems can FLONASE Allergy Relief help with?

FLONASE Allergy Relief helps relieve a broad range of uncomfortable symptoms like congestion and itchy eyes.

Nasal symptoms

Eye symptoms

These symptoms can be triggered by allergens like pollen, mold, dust or pet dander.

Outdoor allergens

Animal allergens

Indoor allergens

IMPORTANT – Peel here for complete Drug Facts label. Children 4-11: do not use for more than 2 months a year.

Be sure to read the Quick Start Guide and Question & Answer Leaflet inside package

TAMPER-EVIDENTfeatures for your protection. The product is packaged in a sealed container. Under the cap and nozzle, each bottle has an aluminum seal around bottle neck. Do not use if any of these features are torn or damaged.

Principal Display Panel

FLONASE

ALLERGY RELIEF

Fluticasone Propionate Nasal Spray 50 mcg Per Spray Allergy Symptom Reliever (Glucocorticoid)*

Non-Drowsy Relief of:

- Nasal congestion
- Itchy, watery eyes
- Itchy nose
- Runny nose
- Sneezing

FULL PRESCRIPTION STRENGTH

24 HOUR RELIEF

0.62 fl oz (18.2 mL)

144 METERED SPRAYS

*Fluticasone propionate is a steroid medicine known as a glucocorticoid.